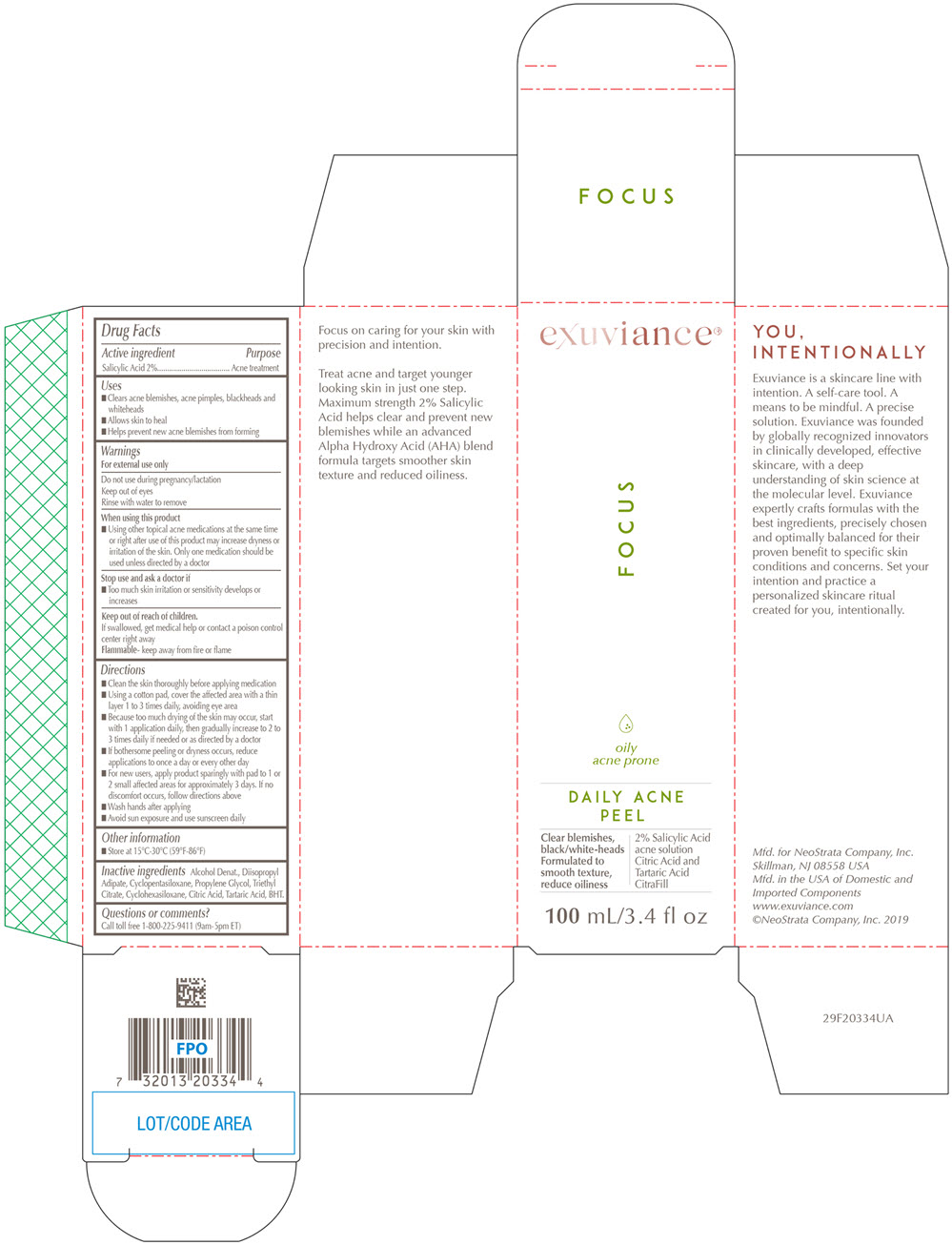 DRUG LABEL: Exuviance Daily Acne Peel
NDC: 58414-0017 | Form: LIQUID
Manufacturer: NeoStrata Company Inc.
Category: otc | Type: HUMAN OTC DRUG LABEL
Date: 20250110

ACTIVE INGREDIENTS: SALICYLIC ACID 20 mg/1 mL
INACTIVE INGREDIENTS: ALCOHOL; DIISOPROPYL ADIPATE; CYCLOMETHICONE 5; TRIETHYL CITRATE; PROPYLENE GLYCOL; CYCLOMETHICONE 6; CITRIC ACID MONOHYDRATE; TARTARIC ACID; BUTYLATED HYDROXYTOLUENE

Exuviance®Daily Acne Peel

Drug Facts

Active ingredient

Salicylic Acid 2%

Purpose

Acne treatment

Uses

- Clears acne blemishes, acne pimples, blackheads and whiteheads
- Allows skin to heal
- Helps prevent new acne blemishes from forming

Warnings

For external use only

Do not use during pregnancy/lactation

keep out of eyes

Rinse with water to remove

When using this product

- Using other topical acne medications at the same time or right after use of this product may increase dryness or irritation of the skin. Only one medication should be used unless directed by a doctor

Stop use and ask a doctor if

- Too much skin irritation or sensitivity develops or increases

Keep out of reach of children.

If swallowed, get medical help or contact a poison control center right away

Flammable-keep away from fire or flame

Directions

- Clean the skin thoroughly before applying medication
- Using a cotton pad, cover the affected area with a thin layer 1 to 3 times daily, avoiding eye area
- Because too much drying of the skin may occur, start with 1 application daily, then gradually increase to 2 to 3 times daily if needed or as directed by a doctor
- If bothersome peeling or dryness occurs, reduce applications to once a day or every other day
- For new users, apply product sparingly with pad to 1 or 2 small affected areas for approximately 3 days. If no discomfort occurs, follow directions above
- Wash hands after applying
- Avoid sun exposure and use sunscreen daily

Other information

- Store at 15°C-30°C (59°F – 86°F)

Inactive ingredients

Alcohol Denat., Diisopropyl Adipate, Cyclopentasiloxane, Propylene Glycol, Triethyl Citrate, Cyclohexasiloxane, Citric Acid, Tartaric Acid, BHT.

Questions or comments?

Call toll free 1-800-225-9411 (9am – 5pm ET)

PRINCIPAL DISPLAY PANEL - 100 mL Bottle Carton

exuviance®

FOCUS

oily
acne prone
DAILY ACNE
PEEL
Clear blemishes,
black/white-heads
Formulated to
smooth texture,
reduce oiliness

2% Salicylic Acid
acne solution
Citric Acid and
Tartaric Acid
CitraFill

100 mL/3.4 fl oz